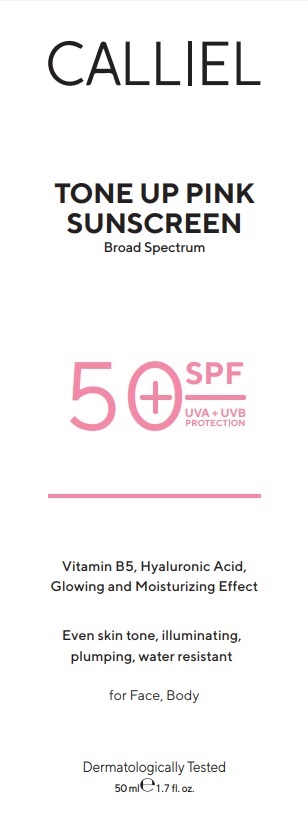 DRUG LABEL: CALLIEL TONE UP PINK SUNSCREEN Broad Spectrum SPF 50
NDC: 87411-0007 | Form: CREAM
Manufacturer: CALLIEL PHARMA KOZMETIK SANAYI VE TICARET ANONIM SIRKETI
Category: otc | Type: HUMAN OTC DRUG LABEL
Date: 20260207

ACTIVE INGREDIENTS: OCTOCRYLENE 5 g/100 g; TITANIUM DIOXIDE 1.8 g/100 g; AVOBENZONE 4.6 g/100 g; ZINC PCA 0.32 g/100 g; HOMOSALATE 4.6 g/100 g; ETHYLHEXYL METHOXYCINNAMATE 8.51 g/100 g
INACTIVE INGREDIENTS: ANHYDROXYLITOL 0.32 g/100 g; 2-ETHYLHEXYL ACRYLATE, METHACRYLATE, METHYL METHACRYLATE, OR BUTYL METHACRYLATE/HYDROXYPROPYL DIMETHICONE COPOLYMER (30000-300000 MW) 1.64 g/100 g; BEHENYL ALCOHOL 0.32 g/100 g; ARACHIDYL GLUCOSIDE 0.18 g/100 g; CAPRYLYL GLYCOL 0.12 g/100 g; TRIETHOXYCAPRYLYLSILANE 0.18 g/100 g; ALOE BARBADENSIS LEAF JUICE 0.12 g/100 g; AQUA 48.2 g/100 g; GLYCERYL STEARATE 3.22 g/100 g; XYLITYLGLUCOSIDE 1.3 g/100 g; PANTHENOL 0.8 g/100 g; GLYCERIN 1.6 g/100 g; ALPHA-ARBUTIN 1.52 g/100 g; PHENOXYETHANOL 0.82 g/100 g; SILICA 0.06 g/100 g; ARACHIDYL ALCOHOL 0.32 g/100 g; XANTHAN GUM 0.16 g/100 g; CETEARETH-20 3.21 g/100 g; BUTYROSPERMUM PARKII (SHEA) BUTTER 1.8 g/100 g; HYALURONIC ACID 0.12 g/100 g; XYLITOL 0.32 g/100 g; DIMETHICONE 1.61 g/100 g; C12-15 ALKYL BENZOATE 5.6 g/100 g; CAPRYLIC/CAPRIC TRIGLYCERIDE 1.63 g/100 g

Aktive ingredients

Ethylhexyl Methoxycinnamate (Octinoxate) 8.51%

Octocrylene 5.00%

Butyl Methoxydibenzoylmethane (Avobenzone) 4.60%

Homosalate 4.60%

Titanium Dioxide 1.80%

Uses

• helps prevent sunburn
• if used as directed with other sun protection measures (see Directions), decreases the risk of skin cancer and early skin aging caused by the sun

Do not use on damaged or broken skin

Stop use and ask a doctor if rash occurs.

Keep out of reach of children. If swallowed, get medical help or contact a Poison Control Center right away.

Directions

• apply liberally 15 minutes before sun exposure
• reapply:
• after 80 minutes of swimming or sweating
• immediately after towel drying
• at least every 2 hours
• children under 6 months: Ask a doctor

Sun Protection Measures: Spending time in the sun increases your risk of skin cancer and early skin aging caused by the sun. To decrease this risk, regularly use a sunscreen with a Broad Spectrum SPF 15 or higher and other sun protection measures including:
• limit time in the sun, especially from 10 a.m. – 2 p.m.
• wear long-sleeve shirts, pants, hats, and sunglasses

Warnings

For external use only

Purpose

Sunscreen

Inactive ingredients

Water, C12-15 Alkyl Benzoate, Cetearyl Alcohol, Glyceryl Stearate, Ceteareth-20, Caprylic/Capric Triglyceride, Butyrospermum Parkii (Shea) Butter, Dimethicone, Acrylates/Dimethicone Copolymer, Glycerin, Alpha-Arbutin, Niacinamide, Panthenol, Hyaluronic Acid, Xylitylglucoside, Anhydroxylitol, Xylitol, Zinc PCA, Arachidyl Alcohol, Behenyl Alcohol, Arachidyl Glucoside, Phenoxyethanol, Caprylyl Glycol, Aloe Barbadensis Leaf Extract, Xanthan Gum, Silica, Triethoxycaprylylsilane.

PACKAGE LABEL

CALLIEL

TONE UP PINK SUNSCREEN
Broad Spectrum SPF 50+

UVA/UVB Protection

Tone-up effect
Helps even skin tone

With Vitamin B5 and Hyaluronic Acid

For Face and Body

Net 1.7 fl oz (50 mL)